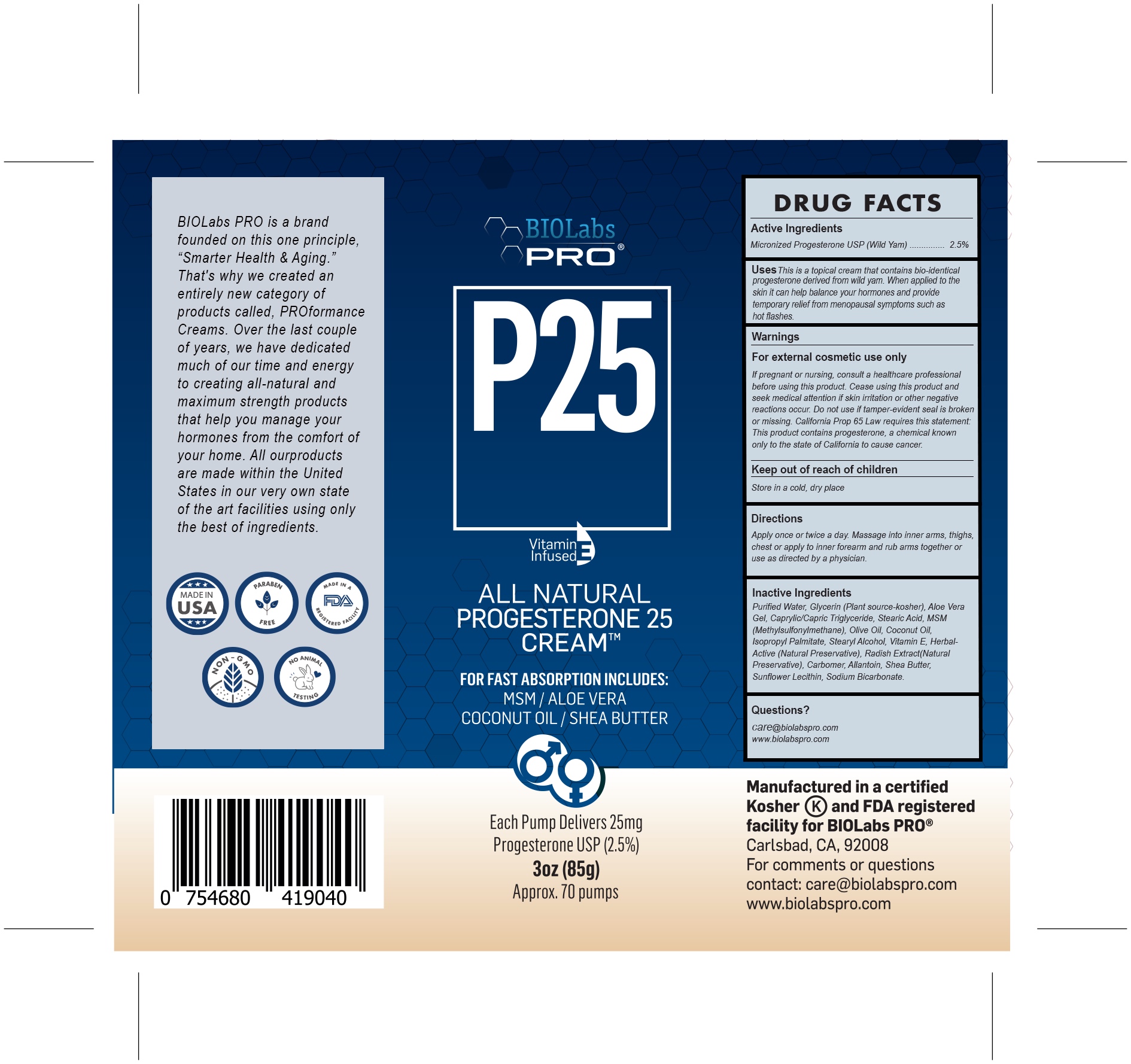 DRUG LABEL: P25 Progesterone Cream
NDC: 82018-0011 | Form: CREAM
Manufacturer: SHYNE BRANDS
Category: otc | Type: HUMAN OTC DRUG LABEL
Date: 20250601

ACTIVE INGREDIENTS: PROGESTERONE 25 mg/85 g
INACTIVE INGREDIENTS: GLYCERIN 1 mg/85 g; ALLANTOIN 1 mg/85 g; OLIVE OIL 1 mg/85 g; COCONUT OIL 1 mg/85 g; STEARIC ACID 1 mg/85 g; ISOPROPYL PALMITATE 1 mg/85 g; LECITHIN, SUNFLOWER 1 mg/85 g; SHEA BUTTER 1 mg/85 g; ALOE VERA LEAF 1 mg/85 g; SODIUM BICARBONATE 1 mg/85 g

P25 Progesterone Cream

DRUG FACTS

Active Ingredients

Micronizrd Progesterone USP (Wild Yam) 2.5%

PURPOSE

This is a topical cream that contains bio-identical progesterone derived from wild yam. When applied to the skin it can help balance your hormones and provide temporary relief from menopausal symptoms such as hot flashes.

INDICATIONS AND USAGE

USES: This is a topical cream that contains bio-identical progesterone derived from wild yam. When applied to the skin it can help balance your hormones and provide temporary relief from menopausal symptoms such as hot flashes.

DIRECTIONS:

Apply once or twice a day. Massage into inner arms, thighs, chest or apply to inner forearm and rub arms together or use as directed by your Physician.

WARNINGS

WARNING: FOR EXTERNAL COSMETIC USE ONLY. Discontinue use if irritation or red skin develops, and consult a Physician. If pregnant, nursing, or if you have a serious medical condition consult a healthcare professional before using this product. Do not use with any other progesterone or progestins. Do not use if tamper-evident seal is broken or missing. California Prop 65 Law requires this statement: This product contains progesterone, a chemical known only to the State of California to cause cancer. Cease using this product and seek medical attention if skin irritation or other negative reactions occur. KEEP OUT OF REACH OF CHILDREN.

PREGNANCY OR BREAST FEEDING

If pregnant or nursing or if you have a serious medical condition consult a healthcare professional before using this product.

Keep Out of Reach of Children.

DOSAGE AND ADMINISTRATION

Apply once or twice a day. Massage into inner arms, thighs, chest or apply to inner forearm and rub arms together or use as directed by you physician.

INACTIVE INGREDIENT

Purified Water Glycerin (Plant source - kosher) Aloe Vera Gel Caprylic/Capric Triglyceride Stearic Acid MSM (Methylsulfonylmethane) Olive Oil Coconut Oil Isopropyl Palmitate Stearyl Alcohol Vitamin E Herbal-Active® (Natural Preservative) Radish Extract (Natural Preservative) Carbomer Allantoin Shea Butter Sunflower Lecithin Retinol (vitamin A) Sodium Bicarbonate

Questions?

care@biolabspro.com

www.biolabspro.com